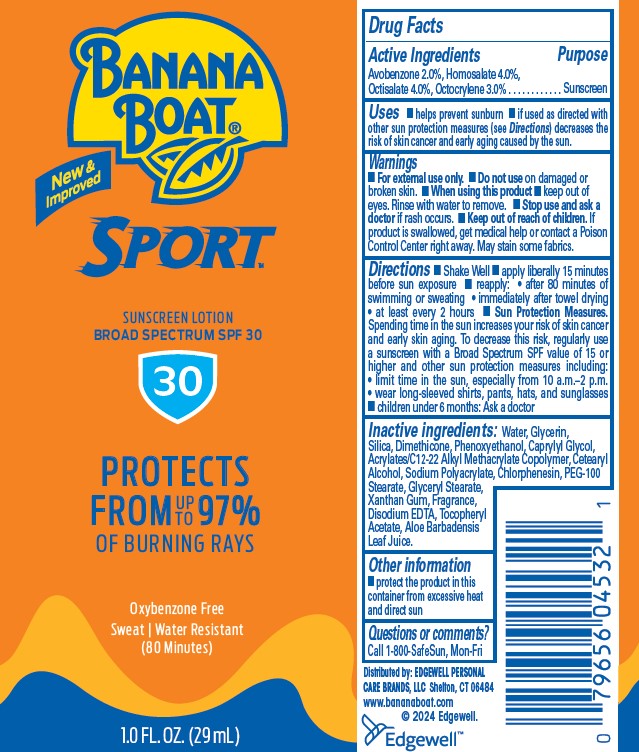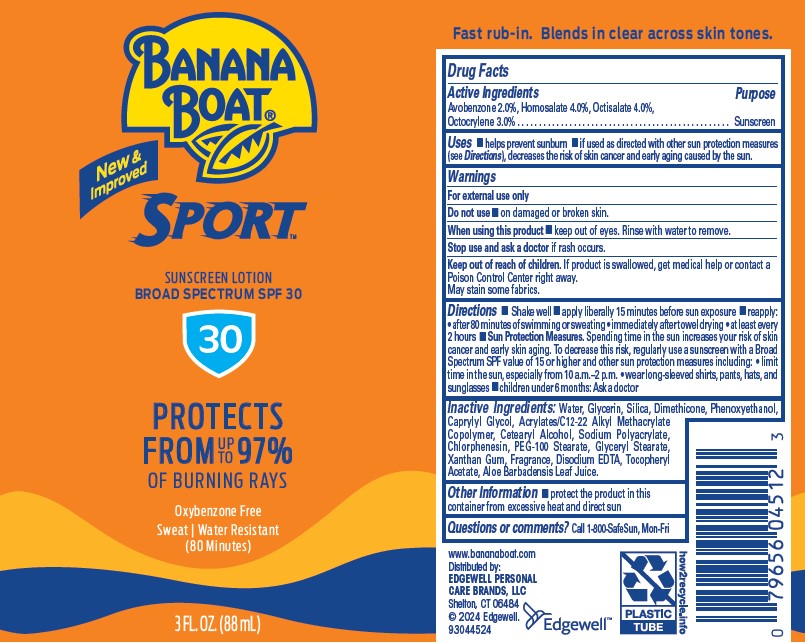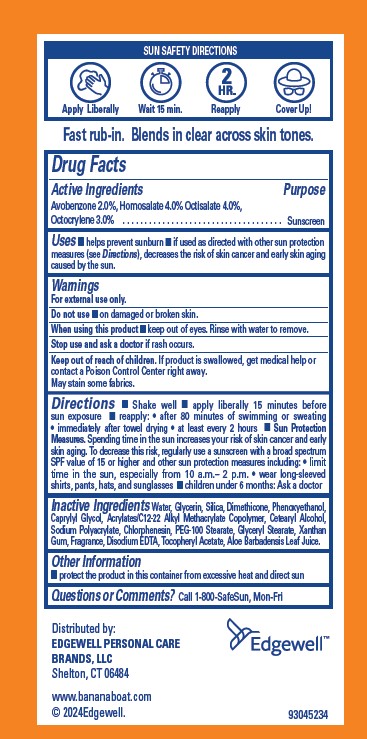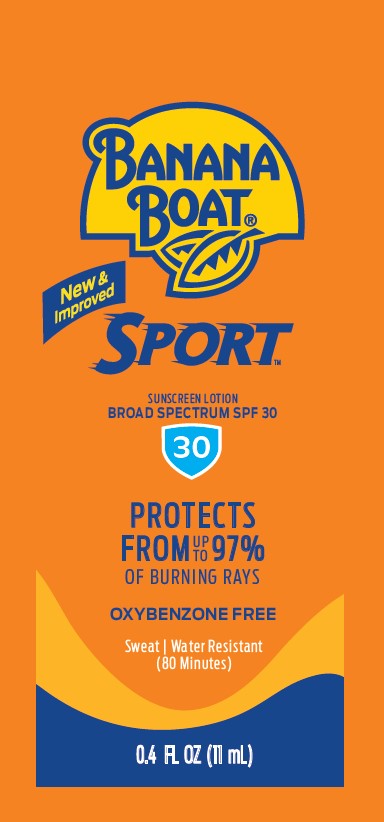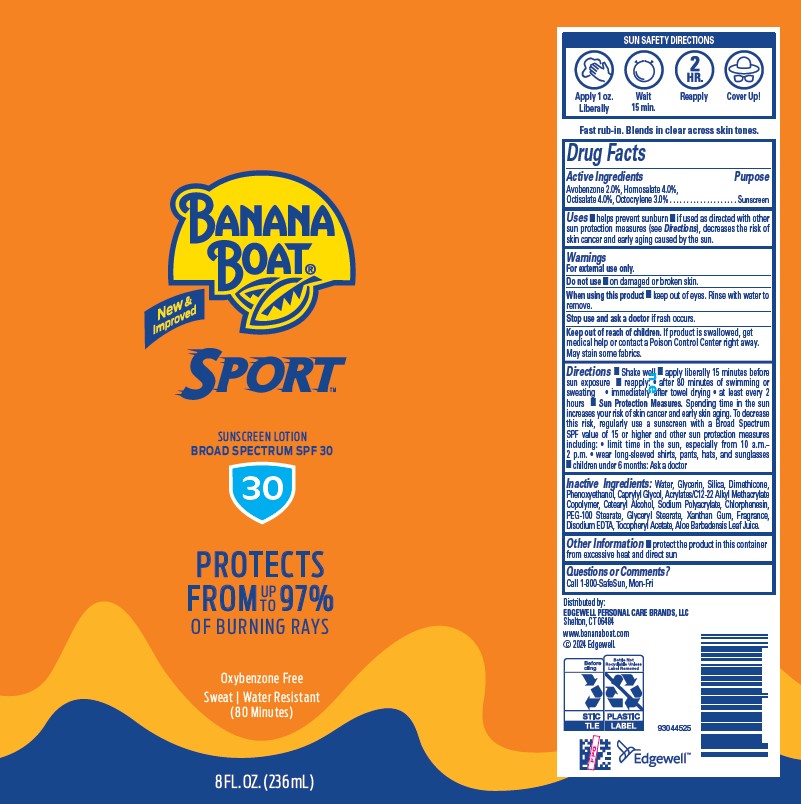 DRUG LABEL: BANANA BOAT
NDC: 63354-131 | Form: LOTION
Manufacturer: Edgewell Personal Care Brands LLC
Category: otc | Type: HUMAN OTC DRUG LABEL
Date: 20251123

ACTIVE INGREDIENTS: HOMOSALATE 4 g/100 g; OCTISALATE 4 g/100 g; OCTOCRYLENE 3 g/100 g; AVOBENZONE 2 g/100 g
INACTIVE INGREDIENTS: DIMETHICONE; SILICON DIOXIDE; CETOSTEARYL ALCOHOL; PEG-100 STEARATE; GLYCERYL MONOSTEARATE; GLYCERIN; SODIUM POLYACRYLATE (2500000 MW); WATER; PHENOXYETHANOL; CAPRYLYL GLYCOL; XANTHAN GUM; EDETATE DISODIUM; ALOE VERA LEAF; CHLORPHENESIN; .ALPHA.-TOCOPHEROL ACETATE

Active Ingredients

Avobenzone 2.0%, Homosalate 4.0% Octisalate 4.0%, Octocrylene 3.0

Purpose

Sunscreen

Uses

• helps prevent sunburn • if used as directed with other sun protection measures (see Directions), decreases the risk of skin cancer and early skin aging caused by the sun.

Warnings

For external use only.

May stain some fabrics.

Do not use

• on damaged or broken skin.

When using this product

• keep out of eyes. Rinse with water to remove.

Stop use and ask a doctor

if rash occurs.

Keep out of reach of children.

If product is swallowed, get medical help or contact a Poison Control Center right away.

Directions

• Shake well • apply liberally 15 minutes before sun exposure • reapply: • after 80 minutes of swimming or sweating • immediately after towel drying • at least every 2 hours • Sun Protection Measures. Spending time in the sun increases your risk of skin cancer and early skin aging. To decrease this risk, regularly use a sunscreen with a broad spectrum SPF value of 15 or higher and other sun protection measures including: • limit time in the sun, especially from 10 a.m.– 2 p.m. • wear long-sleeved shirts, pants, hats, and sunglasses • children under 6 months: Ask a doctor

Inactive Ingrdients

Water, Glycerin, Silica, Dimethicone, Phenoxyethanol, Caprylyl Glycol, Acrylates/C12-22 Alkyl Methacrylate Copolymer, Cetearyl Alcohol, Sodium Polyacrylate, Chlorphenesin, PEG-100 Stearate, Glyceryl Stearate, Xanthan Gum, Fragrance, Disodium EDTA, Tocopheryl Acetate, Aloe Barbadensis Leaf Juice.

Other Information

• protect the product in this container from excessive heat and direct sun

Questions or Comments?

Call 1-800-SafeSun, Mon-Fri

Principal Display Panel

BANANA

BOAT
New &
Improved
SPORT
SUNSCREEN LOTION
BROAD SPECTRUM SPF 30
30
PROTECTS
FROM UP TO 97%
OF BURNING RAYS
OXYBENZONE FREE
Sweat | Water Resistant
(80 Minutes)
0.4 FL OZ (11 mL)

BANANA
BOAT
New &
Improved
SPORT
SUNSCREEN LOTION
BROAD SPECTRUM SPF 30
30
PROTECTS
FROM UP TO 97%
OF BURNING RAYS
Oxybenzone Free
Sweat | Water Resistant
(80 Minutes)
8 FL OZ (236 mL)

BANANA
BOAT
New &
Improved
SPORT
SUNSCREEN LOTION
BROAD SPECTRUM SPF 30
30
PROTECTS
FROM UP TO 97%
OF BURNING RAYS
Oxybenzone Free
Sweat | Water Resistant
(80 Minutes)
1.0 FL OZ (29 mL)

BANANA
BOAT
New &
Improved
SPORT
SUNSCREEN LOTION
BROAD SPECTRUM SPF 30
30
PROTECTS
FROM UP TO 97%
OF BURNING RAYS
Oxybenzone Free
Sweat | Water Resistant
(80 Minutes)
3 FL OZ (88 mL)